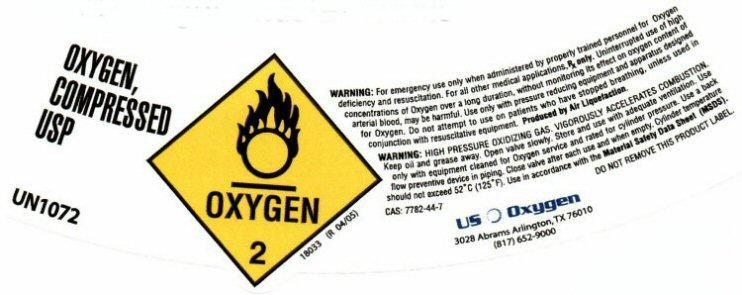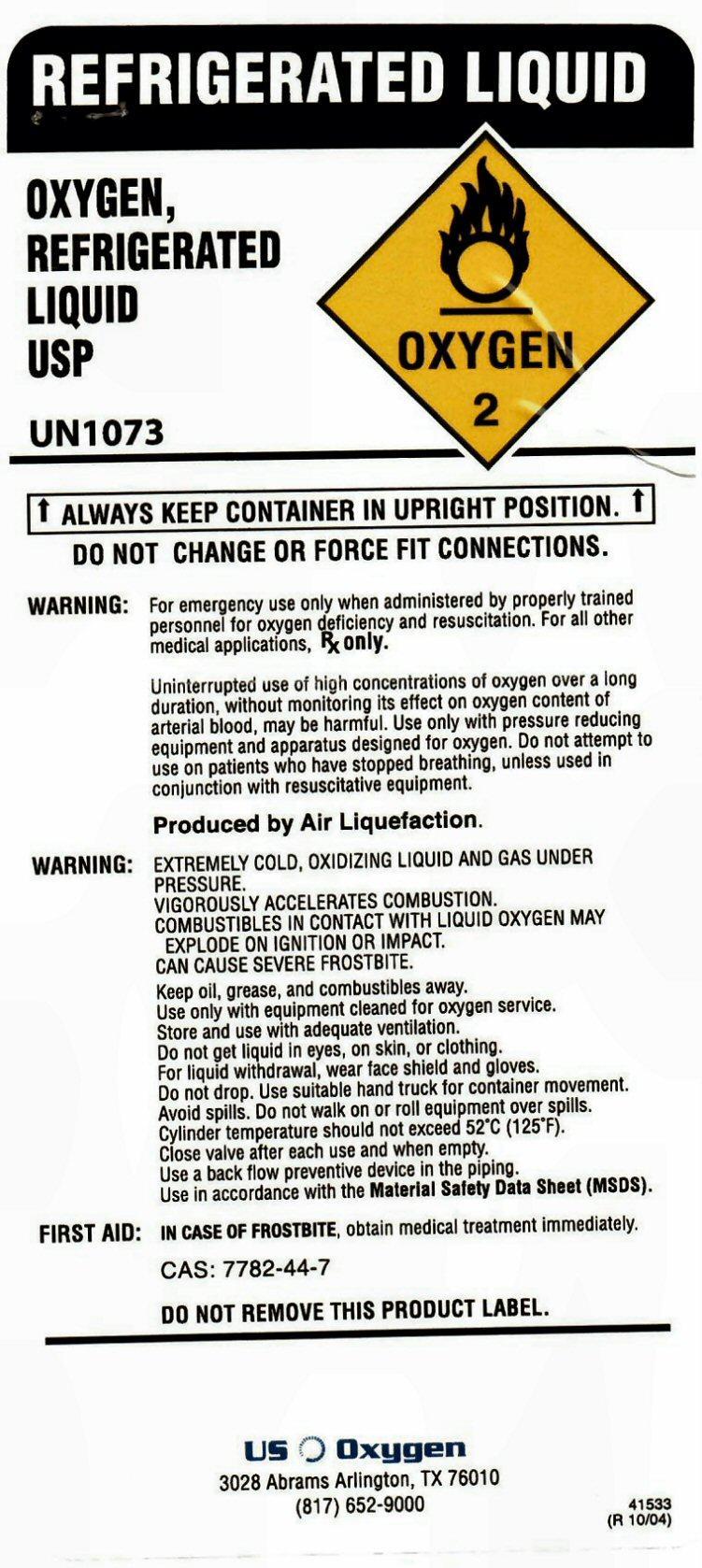 DRUG LABEL: OXYGEN
NDC: 54632-001 | Form: GAS
Manufacturer: U.S. Oxygen and Supply, LLC
Category: prescription | Type: HUMAN PRESCRIPTION DRUG LABEL
Date: 20140221

ACTIVE INGREDIENTS: OXYGEN 99 L/100 L

OXYGEN COMPRESSED USP SL

OXYGEN COMPRESSED USP UN1072 OXYGEN 2 18033 (R 04/05)
WARNING: For emergency use only when administered by properly trained personnel for Oxygen deficiency and resuscitation. For all other medical applications, Rx only. Uninterrupted use of high concentrations of Oxygen over a long duration, without monitoring its effect on oxygen content of arterial blood, may be harmful. Use only with pressure reducing equipment and apparatus designed for Oxygen. Do not attempt to use on patients who have stopped breathing, unless used in conjunction with resuscitative equipment. Produced by Air Liquefaction.

WARNING:HIGH PRESSURE OXIDIZING GAS. VIGOROUSLY ACCELERATES COMBUSTION. Keep oil and grease away. Open valve slowly. Store and use with adequate ventilation. Use only with equipment cleaned for Oxygen service and rated for cylinder pressure. Use a back flow preventive device in the piping. Close valve after each use and when empty. Cylinder temperature should not exceed 52 degrees C (125 degrees F). Use in accordance with the Material Safety Data Sheet (MSDS).
CAS: 7782-44-7 DO NOT REMOVE THIS PRODUCT LABEL

US Oxygen
3028 Abrams Arlington, TX 76010 (817) 652-9000

REFRIGERATED OXYGEN LIQUID USP

REFRIGERATED LIQUID
OXYGEN REFRIGERATE LIQUID USP UN1073 OXYGEN 2
ALWAYS KEEP CONTAINER IN UPRIGHT POSITION.
DO NOT CHANGE OR FORCE FIT CONNECTIONS.
WARNING: For emergency use only when administered by properly trained personnel for oxygen deficiency and resuscitation. For all other medical applications Rx only.
Uninterrupted use of high concentrations of oxygen over a long duration, without monitoring its effect on oxygen content of arterial blood, may be harmful. Use only with pressure reducing equipment and apparatus designed for oxygen. Do not attempt to use on patients who have stopped breathing, unless used in conjunction with resuscitative equipment.
Produced by Air Liquefaction.
WARNING: EXTREMELY COLD, OXIDIZING LIQUID AND GAS UNDER PRESSURE.
VIGOROUSLY ACCELERATES COMBUSTION.
COMBUSTIBLES IN CONTACT WITH LIQUID OXYGEN MAY EXPLODE OR IGNITION OR IMPACT.
CAN CAUSE SEVERE FROSTBITE.
Keep oil, grease, and combustibles away.
Use only with equipment cleaned for oxygen service.
Store and use with adequate ventilation.
Do not get liquid in eyes, on skin, or clothing.
For liquid withdraw, wear face shield and gloves.
Do not drop. Use suitable hand truck for container movement.
Avoid spills. Do not walk on or roll equipment over spills.
Cylinder temperature should not exceed 52° C (125° F).
Close valve after each use and when empty.
Use a back flow preventive device in the piping.
Use in accordance with the Material Safety Data Sheet (MSDS).
FIRST AID: IN CASE OF FROSTBITE, obtain medical treatment immediately.

CAS: 7782-44-7

DO NOT REMOVE THIS PRODUCT LABEL

US OXYGEN
3028 Abrams Arlington, TX 76010 (817) 652-9000

41533 (R 10/04)